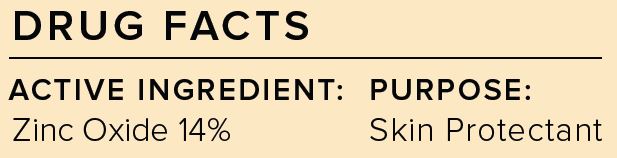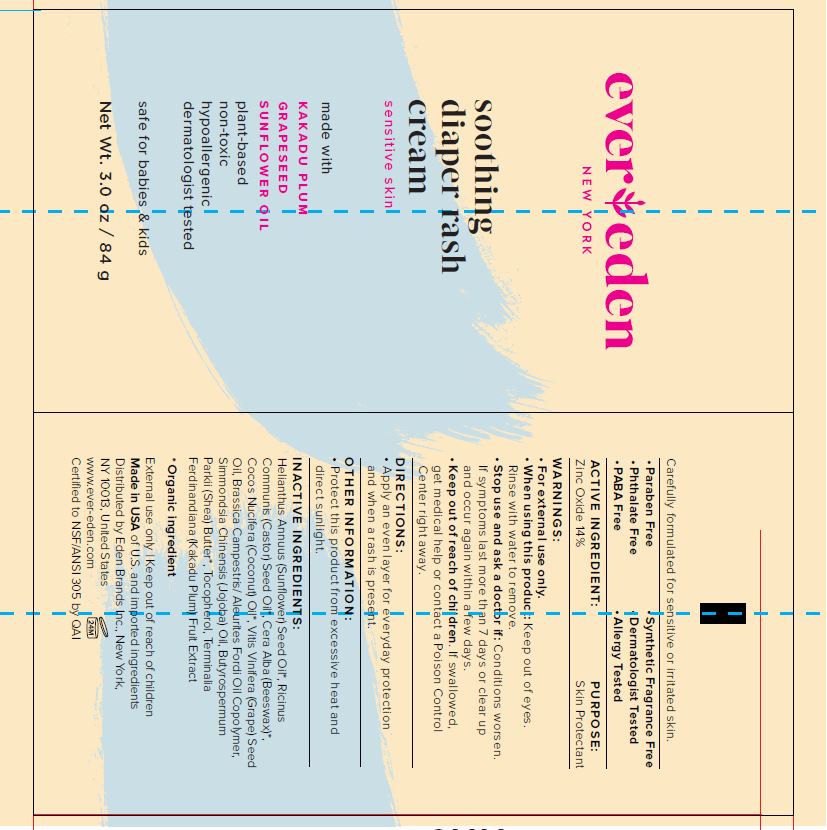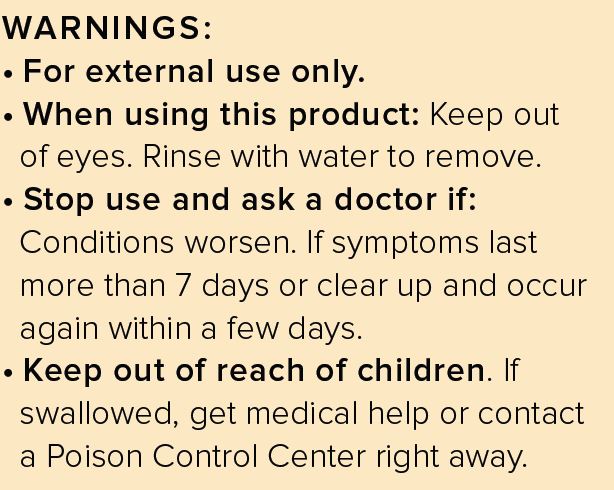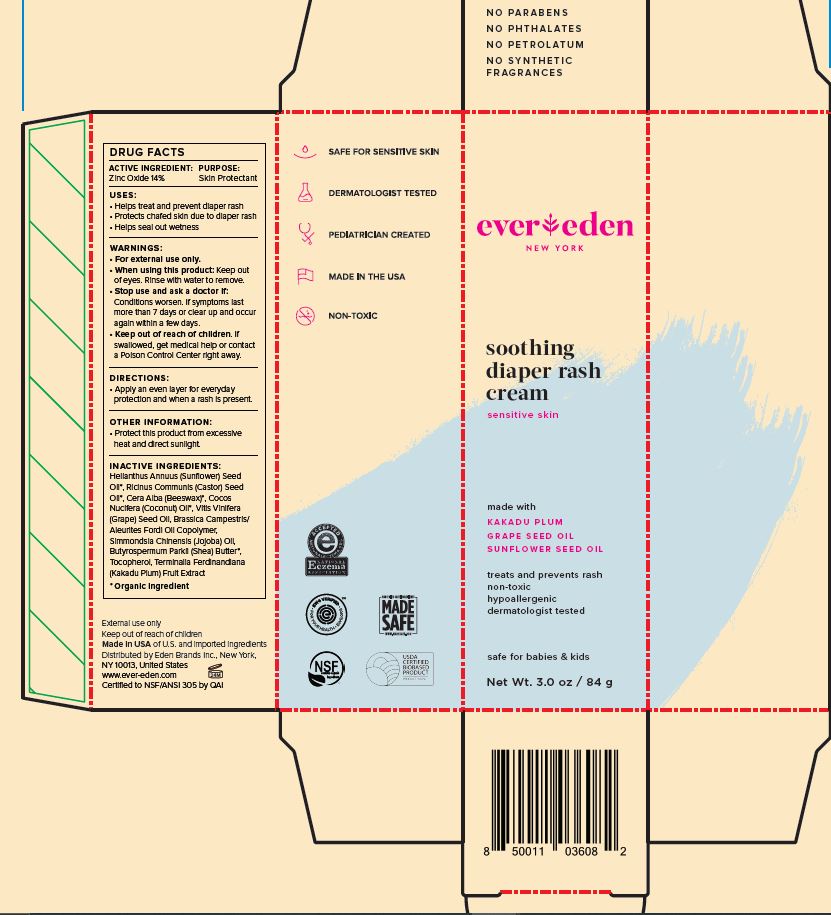 DRUG LABEL: Diaper Cream
NDC: 62932-167 | Form: OINTMENT
Manufacturer: Private Label Select Ltd CO
Category: otc | Type: HUMAN OTC DRUG LABEL
Date: 20220104

ACTIVE INGREDIENTS: ZINC OXIDE 14 g/100 g
INACTIVE INGREDIENTS: KAKADU PLUM; CASTOR OIL; WHITE WAX; COCONUT OIL; JOJOBA OIL; SUNFLOWER OIL; GRAPE SEED OIL; SHEA BUTTER; TOCOPHEROL

Ever Eden Soothing Diaper Cream